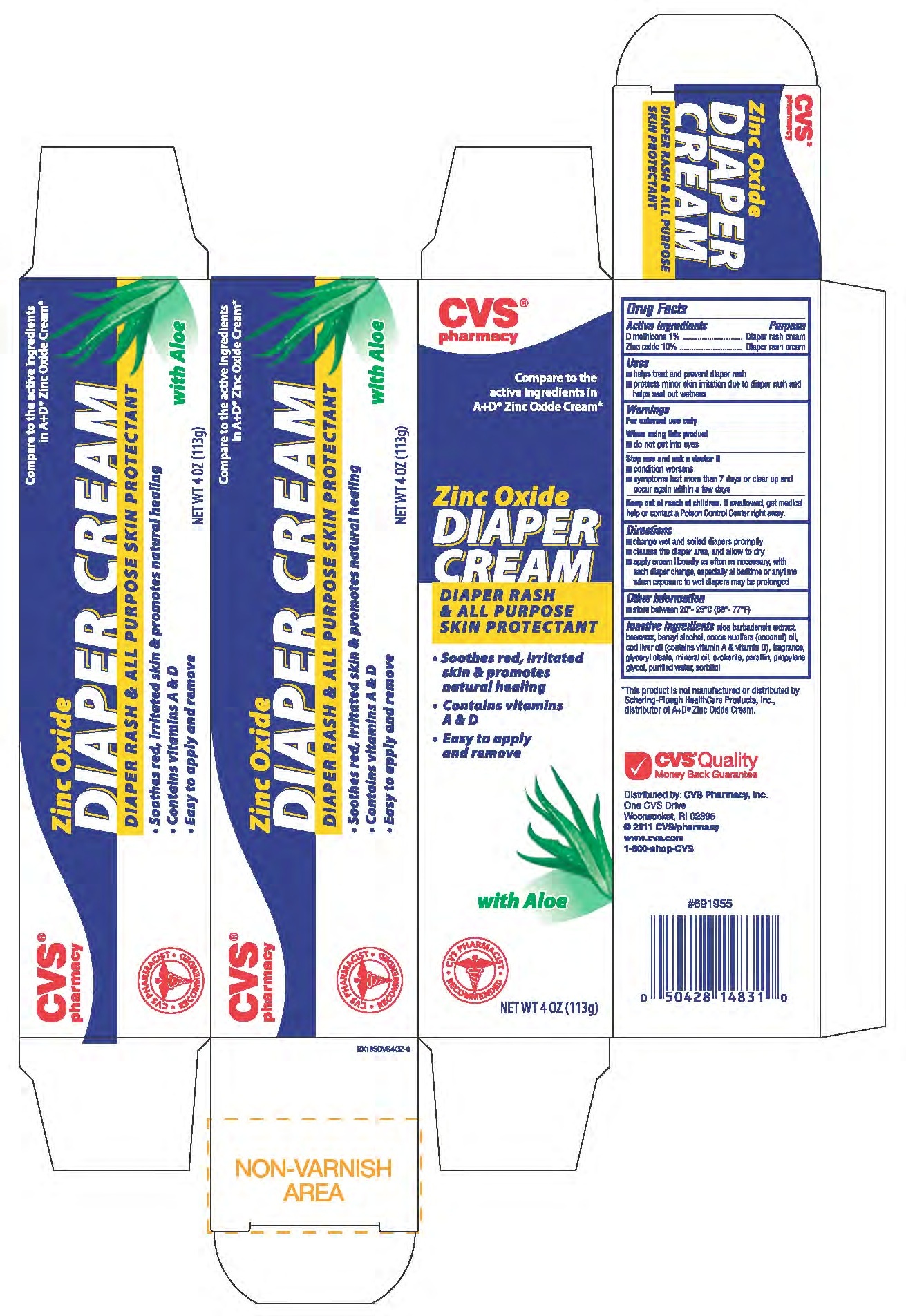 DRUG LABEL: DIMETHICONE and ZINC OXIDE
NDC: 59779-082 | Form: OINTMENT
Manufacturer: CVS
Category: otc | Type: HUMAN OTC DRUG LABEL
Date: 20110216

ACTIVE INGREDIENTS: DIMETHICONE 10 mg/1 g; ZINC OXIDE 100 mg/1 g
INACTIVE INGREDIENTS: WATER; MINERAL OIL; COCONUT OIL; COD LIVER OIL; GLYCERYL MONOOLEATE; PARAFFIN; CERESIN; PROPYLENE GLYCOL; WHITE WAX; BENZYL ALCOHOL; ALOE; SORBITOL

drug facts

Active ingredients Purpose
Dimethicone 1%........................Diaper rash cream
Zinc Oxide 10%........................Diaper rash cream

Active ingredients Purpose
Dimethicone 1%........................Diaper rash cream
Zinc Oxide 10%........................Diaper rash cream

Keep out of reach of children. If swallowed, get medical
help or contact a Poison Control Center right away.

Uses
- helps treat and prevent diaper rash
- protects minor skin irritation due to diaper rash and
helps seal out wetness

Warnings
For external use only.
When using this product
- do not get into eyes
Stop use and ask a doctor if:
- condition worsens
- symptoms last more than 7 days or clear up and
occur again within several days

Directions
- change wet and soiled diapers promptly
- cleanse the diaper area and allow to dry
- apply cream liberally as often as necessary with
each diaper change, especially at bedtime or anytime
when exposure to wet diapers may be prolonged
Other information
Store between 20 degrees to 25 degrees C (68 degrees to 77 degrees F)

Inactive Ingredients aloe barbadensis extract,
benzyl alcohol, coconut oil, cod liver oil (contains
vitamin A and vitamin D), fragrance, glyceryl oleate, light
mineral oil, ozokerite, paraffin, propylene glycol,
sorbitol, synthetic beeswax, water